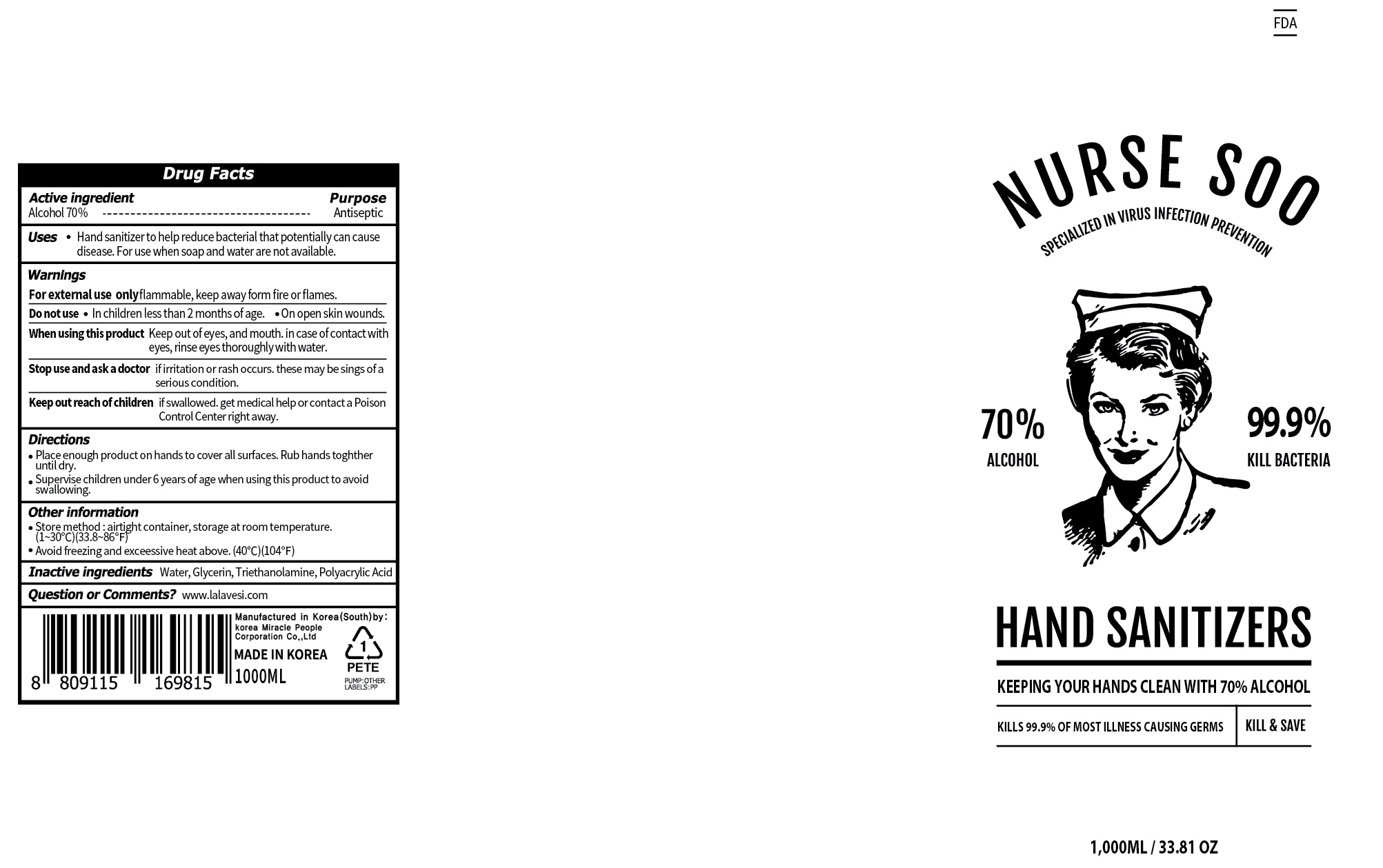 DRUG LABEL: NURSE SOO 70 Hand Sanitizer
NDC: 74082-020 | Form: GEL
Manufacturer: KB Pacific Co., ltd.
Category: otc | Type: HUMAN OTC DRUG LABEL
Date: 20200701

ACTIVE INGREDIENTS: ALCOHOL 700 mL/1000 mL
INACTIVE INGREDIENTS: Water; Glycerin; TROLAMINE

ACTIVE INGREDIENT

ALCOHOL 70%

INACTIVE INGREDIENT

Water, Glycerin, Triethanolamine, Polyacrylic Acid

PURPOSE

Antiseptic

WARNINGS

For extemal use only flammable, keep away form fire or flames.

Do not use

In children less then 2 months of age. On open skin wounds.

When using this product

keep out of eyes, and mouth. In case of contact with eyes, rinse eyes thoroughly with water.

Stop use and ask a doctor if irritation or rash occurs. These may be sings of a serious condition.

KEEP OUT OF REACH OF CHILDREN

if swallowed, get medical help or contaxt a Poison Control Center right away.

Uses

Hand sanitizer to help reduce bacterial that potentially can cause disease.

For use when soap and water are not available.

Directions

Place enough product on hands to cover all surfaces. Rub hands toghther until dry.
Supervise children under 6 years of age shen using this product to avoid swallowing.

Other information

Store method: airtight container, storage at room temperature.
(1~30C)(33.8~86F)
Avoid freezing and excessive heat above.(40C)(104F)

Questions or Comments?

www.lalavesi.com